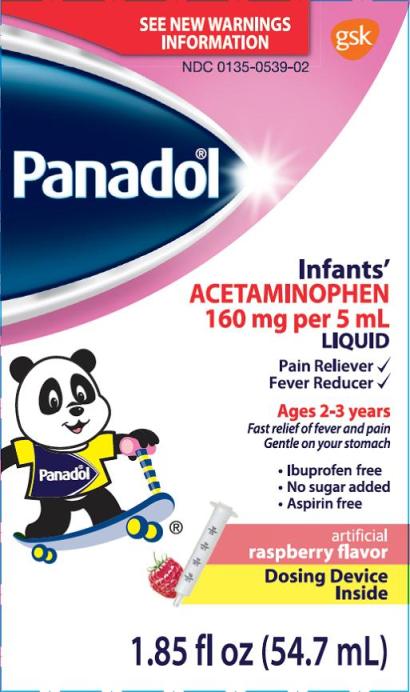 DRUG LABEL: PANADOL
NDC: 0135-0539 | Form: SUSPENSION
Manufacturer: Haleon US Holdings LLC
Category: otc | Type: HUMAN OTC DRUG LABEL
Date: 20240206

ACTIVE INGREDIENTS: ACETAMINOPHEN 160 mg/5 mL
INACTIVE INGREDIENTS: BENZOIC ACID; FD&C RED NO. 40; GLYCERIN; HYDROCHLORIC ACID; POLYETHYLENE GLYCOL, UNSPECIFIED; POTASSIUM SORBATE; PROPYLENE GLYCOL; WATER; SODIUM HYDROXIDE; SACCHARIN SODIUM; SORBITOL

Drug Facts

Active ingredient (in each 5 mL)

Acetaminophen 160 mg

Purposes

Pain reliever/fever reducer

Uses

- temporarily relieves minor aches and pains due to:
  - colds
  - flu
  - headache
  - toothache
- temporarily reduces fever

Warnings

Liver warning:This product contains acetaminophen. Severe liver damage may occur if your child takes

- more than 5 doses in 24 hours, which is the maximum daily amount
- with other drugs containing acetaminophen

Allergy alert:acetaminophen may cause severe skin reactions. Symptoms may include:

- skin reddening
- blisters
- rash

If a skin reaction occurs, stop use and seek medical help right away.

Do not use

- with any other drug containing acetaminophen (prescription or nonprescription). If you are not sure whether a drug contains acetaminophen, ask a doctor or pharmacist.
- if you are allergic to acetaminophen or any of the inactive ingredients in this product

Ask a doctor before use if your child has

liver disease

Ask a doctor or pharmacist before use if your child is

taking the blood thinning drug warfarin

Stop use and ask a doctor if

- pain gets worse or lasts more than 5 days
- fever gets worse or lasts more than 3 days
- redness or swelling is present
- any new symptoms appear

These could be signs of a serious condition.

Overdose warning:

Taking more than the recommended dose can cause serious health problems. In case of overdose, get medical help or contact a Poison Control Center right away. Quick medical attention is critical even if you do not notice any signs or symptoms.

Directions:

this product does not contain directions or complete warnings for adult use

- do not take more than directed(see overdose warning)
- find right dose in chart. If possible use weight to dose; otherwise, use age
- if needed, repeat dose every 4 hours while symptoms persist or as directed by a doctor
- do not take more than 5 doses in 24 hours, unless directed by a doctor
- use only with enclosed pre-marked measuring syringe for accuracy. Do not use any other dosing device.

Age | Weight | Dosage
under 2 yrs | under 24 lbs | ask a doctor
2-3 yrs | 24-35 lbs | 5 mL

Other information

- store below 30°C (86°F)

Inactive ingredients

benzoic acid, FD&C red no. 40, flavor, glycerin, hydrochloric acid*, polyethylene glycol, potassium sorbate, propylene glycol, purified water, sodium hydroxide*, sodium saccharin, sorbitol solution * contains one or more of these ingredients

Questions or comments?

1-800-455-7139(English/Spanish) weekdays

Keep Carton

Principal Display Panel

NDC 0135-0539-02

Panadol®

Infants’

ACETAMINOPHEN

160 mg per 5 mL

LIQUID

Pain Reliever

Fever Reducer

SEE NEW WARNINGS INFORMATION

Ages 2-3 years

Fast relief of fever and pain

Gentle on your stomach

- Ibuprofen free
- No sugar added
- Aspirin free

artificial

raspberry flavor

Dosing Device Inside

l.85 fl oz (54.7 mL)

Tamper Evident Feature:Do not use if printed overwrap is missing or broken.

READ AND KEEP CARTON FOR COMPLETE INFORMATION

GlaxoSmithKlineConsumer Healthcare, L.P.

Moon Township, PA 15108

Made in Canada

©2015 GSK

All Rights Reserved.

USING THE CONVENIENT DOSING DEVICE

- Shake the bottle well. Push the dosing device firmly into the bottle’s neck.
- Turnthe bottle upside down. Holding the device in place, gently pull the plunger out to draw the correct dose.
- With the bottle in an upright position, remove the device from the plug and bottle by gently pullingit. Place the end of the device into the child’s mouth. Administer dose by pressing the plunger slowly.

After use, replace the cap. Washthe device in warm water and allow to dry.

PANADOL, the Beacon design and the Bear design are registered trademarks of the GSK group of companies.

Keep Carton

102012XB (A134044)